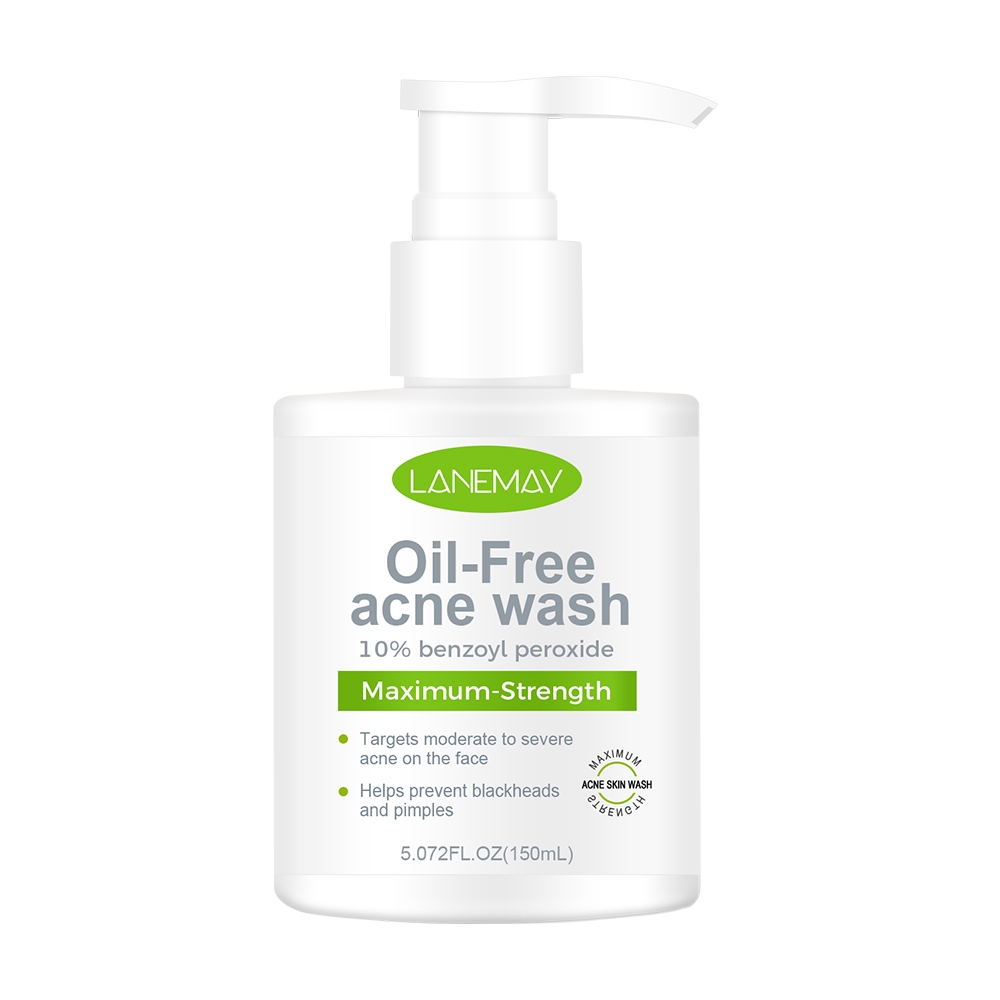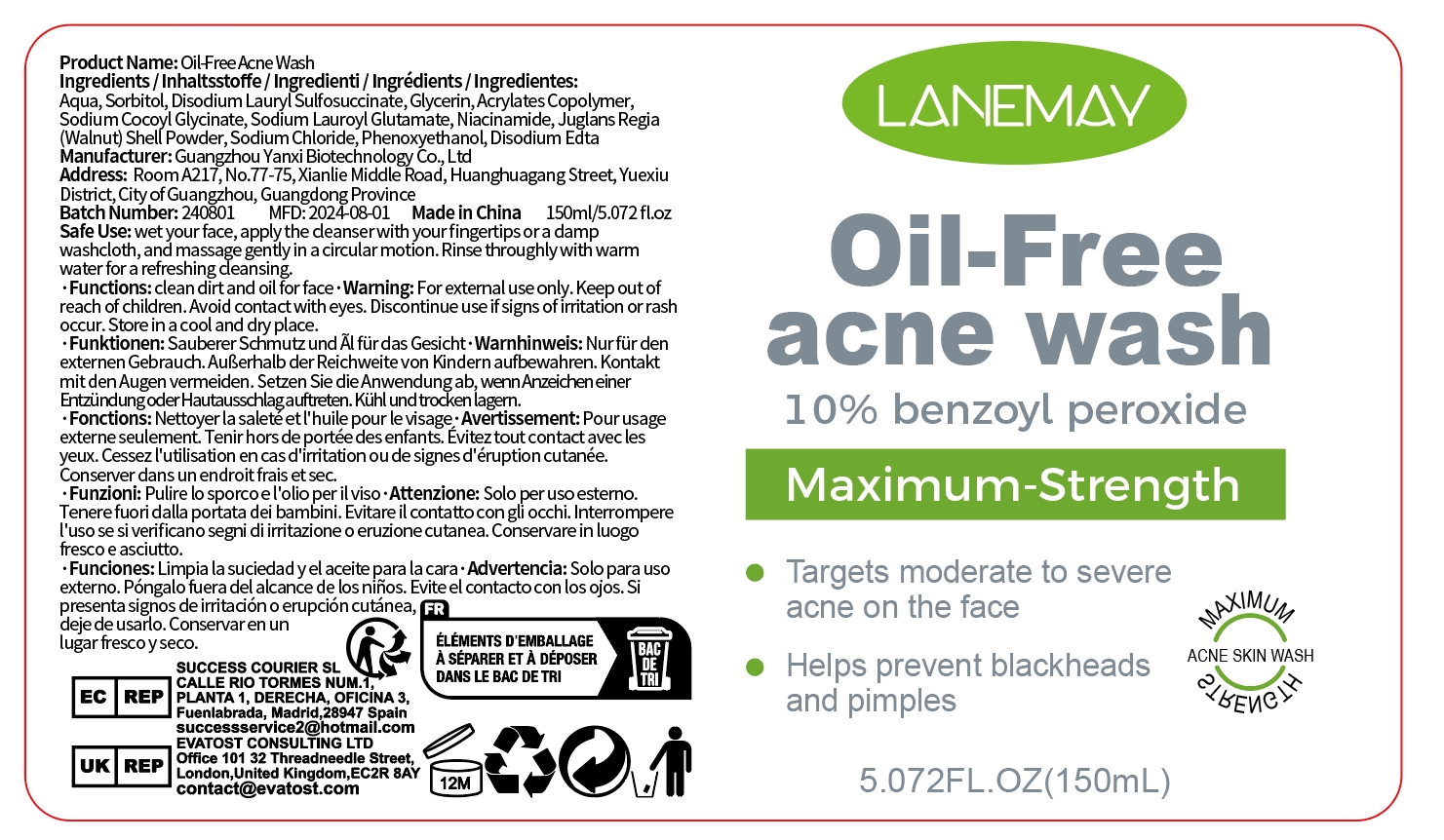 DRUG LABEL: Oil-Free Acne Wash
NDC: 84025-233 | Form: CREAM
Manufacturer: Guangzhou Yanxi Biotechnology Co., Ltd
Category: otc | Type: HUMAN OTC DRUG LABEL
Date: 20241025

ACTIVE INGREDIENTS: SORBITOL 7 mg/150 mL; PHENOXYETHANOL 6 mg/150 mL
INACTIVE INGREDIENTS: WATER

DOSAGE AND ADMINISTRATION

Wet your face,apply the deanser with your fingertips or a damp washcloth,and massage gently in a circular motion.Rinse throughly with warm water for a refreshing deansing.

WARNINGS

Keep out of children

INACTIVE INGREDIENT

Aqua

INDICATIONS AND USAGE

For daily skin wash

Keep out of children

PURPOSE

Helps prevent blackheads and pimples